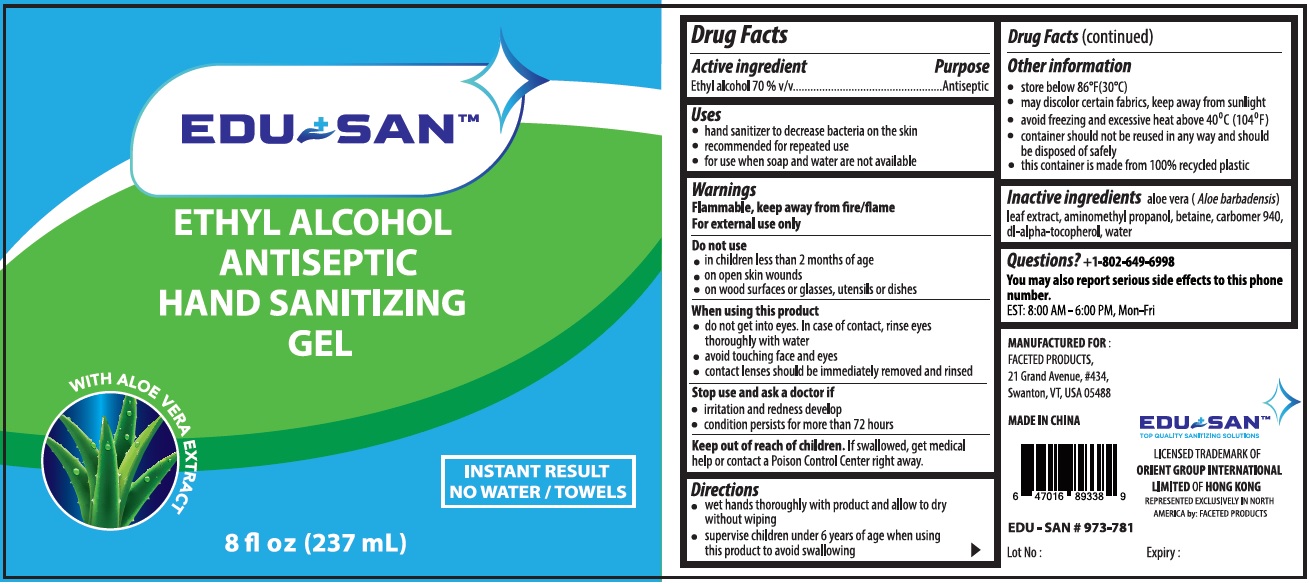 DRUG LABEL: EDU SAN
NDC: 77829-002 | Form: GEL
Manufacturer: Quanzhou Zhezhixin Biochemical Technology Co., LTD
Category: otc | Type: HUMAN OTC DRUG LABEL
Date: 20210308

ACTIVE INGREDIENTS: ALCOHOL 70 mL/100 mL
INACTIVE INGREDIENTS: ALOE VERA LEAF; AMINOMETHYLPROPANOL; BETAINE; CARBOMER HOMOPOLYMER TYPE C (ALLYL PENTAERYTHRITOL CROSSLINKED); .ALPHA.-TOCOPHEROL, DL-; WATER

EDU + SANTM ETHYL ALCOHOL ANTISEPTIC HAND SANITIZING GEL

Active ingredient

Ethyl alcohol 70 % v/v

Purpose

Antiseptic

Uses

• hand sanitizer to decrease bacteria on the skin
• recommended for repeated use
• for use when soap and water are not available

Warnings

Flammable, keep away from fire/flame
For external use only

Do not use

• in children less than 2 months of age

• on open skin wounds

• on wood surfaces or glasses, utensils or dishes

When using this product

• do not get into eyes. In case of contact, rinse eyes thoroughly with water
• avoid touching face and eyes
• contact lenses should be immediately removed and rinsed

Stop use and ask a doctor if

• irritation and redness develop
• condition persists for more than 72 hours

Keep out of reach of children. If swallowed, get medical help or contact a Poison Control Center right away.

Directions

• wet hands thoroughly with product and allow to dry without wiping
• supervise children under 6 years of age when using this product to avoid swallowing

Other information

• store below 86°F(30°C)

• may discolor certain fabrics, keep away from sunlight

• avoid freezing and excessive heat above 40⁰C (104⁰F)

• container should not be reused in any way and should be disposed of safely

• this container is made from 100% recycled plastic

Inactive ingredients

aloe vera (Aloe barbadensis) leaf extract, aminomethyl propanol, betaine, carbomer 940, dl-alpha-tocopherol, water

Questions? +1-802-649-6998

You may also report serious side effects to this phone number.

EST: 8:00 AM - 6:00 PM, Mon-Fri

ETHYL ALCOHOL ANTISEPTIC HAND SANITIZING GEL

WITH ALOE VERA EXTRACT

INSTANT RESULT

NO WATER / TOWELS

MANUFACTURED FOR :
FACETED PRODUCTS,
21 Grand Avenue, #434,
Swanton, VT, USA 05488

MADE IN CHINA

EDU - SAN # 973-781

TOP QUALITY SANITIZING SOLUTIONS

LICENSED TRADEMARK OF ORIENT GROUP INTERNATIONAL LIMITED OF HONG KONG

REPRESENTED EXCLUSIVELY IN NORTH AMERICA by: FACETED PRODUCTS